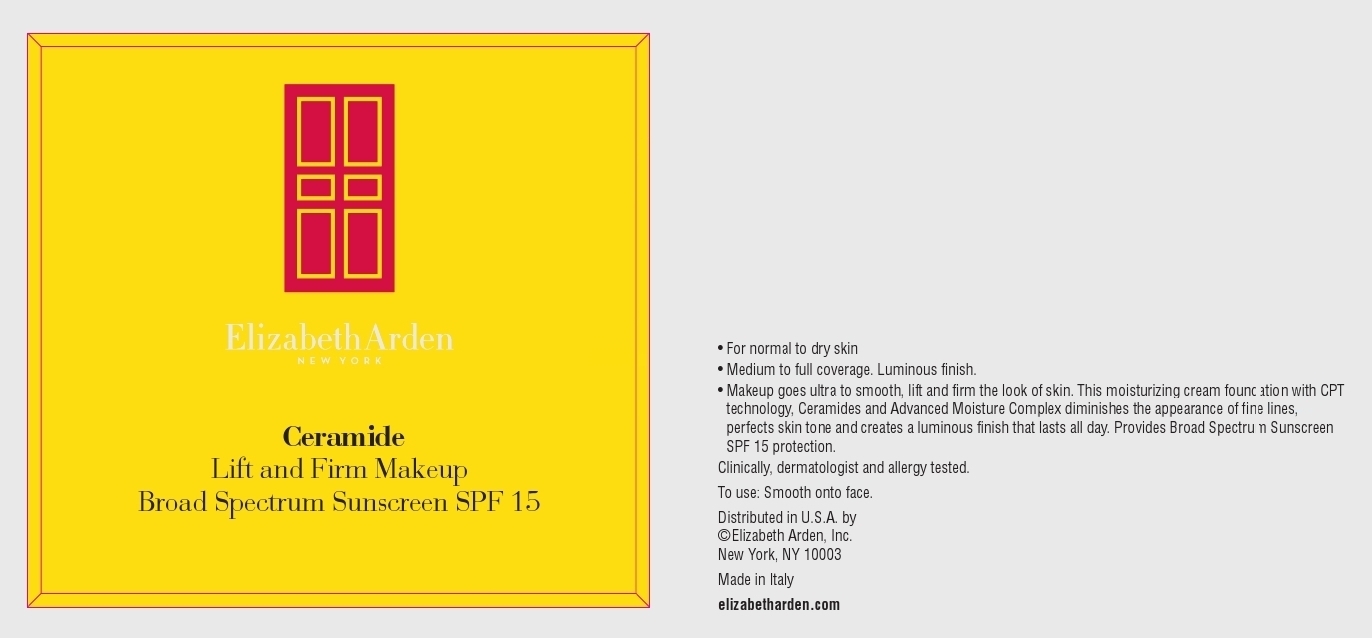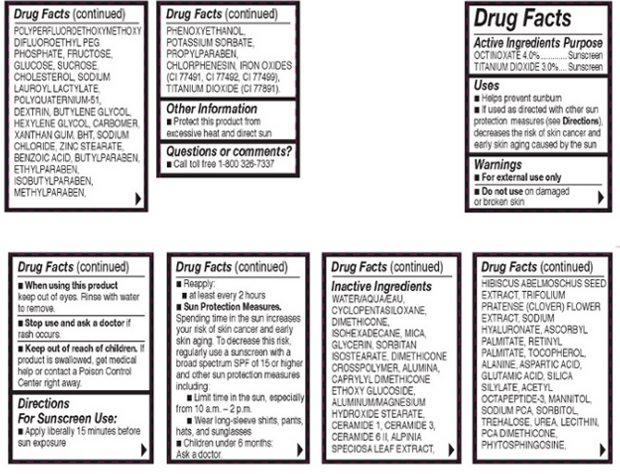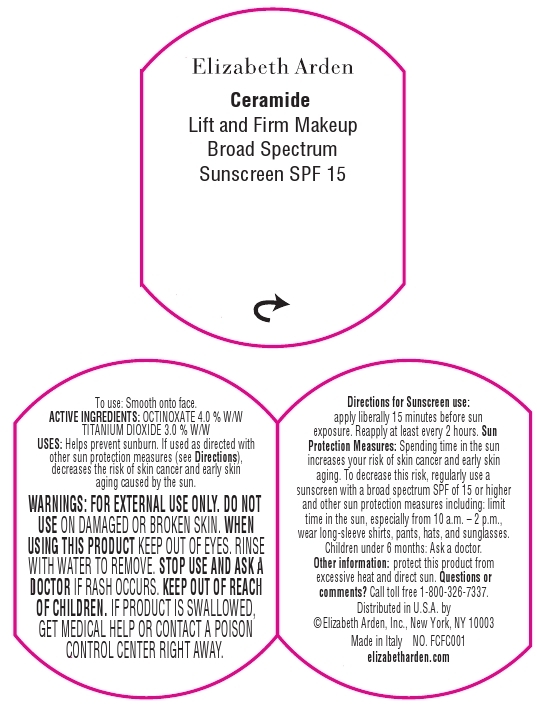 DRUG LABEL: Ceramide Lift And Firm Makeup Broad Spectrum Sunscreen SPF 15 Cream
NDC: 67938-0940 | Form: CREAM
Manufacturer: Elizabeth Arden, Inc
Category: otc | Type: HUMAN OTC DRUG LABEL
Date: 20130708

ACTIVE INGREDIENTS: OCTINOXATE 1.28 g/32 g; TITANIUM DIOXIDE 0.96 g/32 g
INACTIVE INGREDIENTS: WATER; DIMETHICONE; ISOHEXADECANE; MICA; GLYCERIN; CERAMIDE 3; TRIFOLIUM PRATENSE FLOWER; ASCORBYL PALMITATE; ALANINE; ASPARTIC ACID; GLUTAMIC ACID; MANNITOL; SORBITOL; TREHALOSE; UREA; FRUCTOSE; SUCROSE; CHOLESTEROL; SODIUM LAUROYL LACTYLATE; BUTYLENE GLYCOL; HEXYLENE GLYCOL; XANTHAN GUM; SODIUM CHLORIDE; ZINC STEARATE; BENZOIC ACID; BUTYLPARABEN; ETHYLPARABEN; ISOBUTYLPARABEN; METHYLPARABEN; PHENOXYETHANOL; POTASSIUM SORBATE; PROPYLPARABEN; CHLORPHENESIN

BB0940

DESCRIPTION

- For normal to dry skin.

- Medium to full coverage. Luminous finish.

Makeup goes ultra to smooth, lift, and firm the look of skin. This moisturizing cream foundation with CPT technology, Ceramides, and Advanced Moisture Complex diminished the appearance of fine lines, perfects skin tone, and creates a luminous finish that lasts all day. Provides Broad Spectrum Sunscreen SPF 15 protection.

INDICATIONS AND USAGE

To Use: Smooth onto face.

For Sunscreen Use: Apply liberally 15 minutes before sun exposure. Reapply at least every 2 hours.

Sun Protection Measures: Spending time in the sun increases your risk of skin cancer and early skin aging. To decrease this risk, regularly use a sunscreen with a broad spectrum SPF of 15 or higher and other sun protection measures including: Limit time in the sun, especially from 10 a.m. - 2 p.m. Wear long-sleeve shirts, pants, hats, and sunglasses.

WARNINGS

For external use only.

Do not use on damaged or broken skin.

When using this product, keep out of eyes. Rinse with water to remove.

Stop use and ask a doctor if rash occurs.

OTC - ACTIVE INGREDIENT

Active Ingredients: Octinoxate 4.0%, Titanium Dioxide 3.0%

INACTIVE INGREDIENT

Other Ingredients: Water/Aqua/Eau, Cyclopentasiloxane, Dimethicone, Isohexadecane, Mica, Glycerin, Sorbitan, Isostearate, Dimethicone Crosspolymer, Alumina, Caprylyl Dimethicone Ethoxy Glucoside, Aluminum/Magnesium Hydroxide Stearate, Ceramide 1, Ceramide 3, Ceramide 6 II, Alpinia Speciosa Leaf Extract, Hibiscus Abelmoschus Seed Extract, Trifolium Pratense (Clover) Flower Extract, Sodium Hyaluronate, Ascorbyl Palmitate, Retinyl palmitate, Tocopherol, Alanine, Aspartic Acide, Glumatic Acid, Silica Silyate, Acetyl Octatpeptide-3, Mannitol, Sodium PCA, Sorbitol, Trehalose, Urea, Lecithin, PCA Dimethicone, Phytosphingosine, Polyperfluoroethoxymethoxy Difluororethyl PEG Phostphate, Fructose, Glucose, Sucrose, Cholesterol, Sodium Lauroyl Lactylate, Polyquaternium-51, Dextrin, Butylene Glycol, Hexylene Glycol, Carbomer, Xanthan Gum, BHT, Sodium Choloride, Zinc Stearate, Benzoic Acid, Butylparaben, Ethylparaben, Isobutylparaben, Methylparaben, Phenoxyethanol, Pottasium Sorbate, Propylparaben, Chlorphenesin, Iron Oxides (CI 77481, CI 77482), Titanium Dioxide (CI 77891).

DOSAGE & ADMINISTRATION

Smooth on to face.

OTC - KEEP OUT OF REACH OF CHILDREN

Keep out of reach of children. If product is swallowed, get medical help or contact a Poison Control Center right away.

OTC - PURPOSE

Provides SPF 15 sun protection.

OTC - WHEN USING

Keep out of eyes.